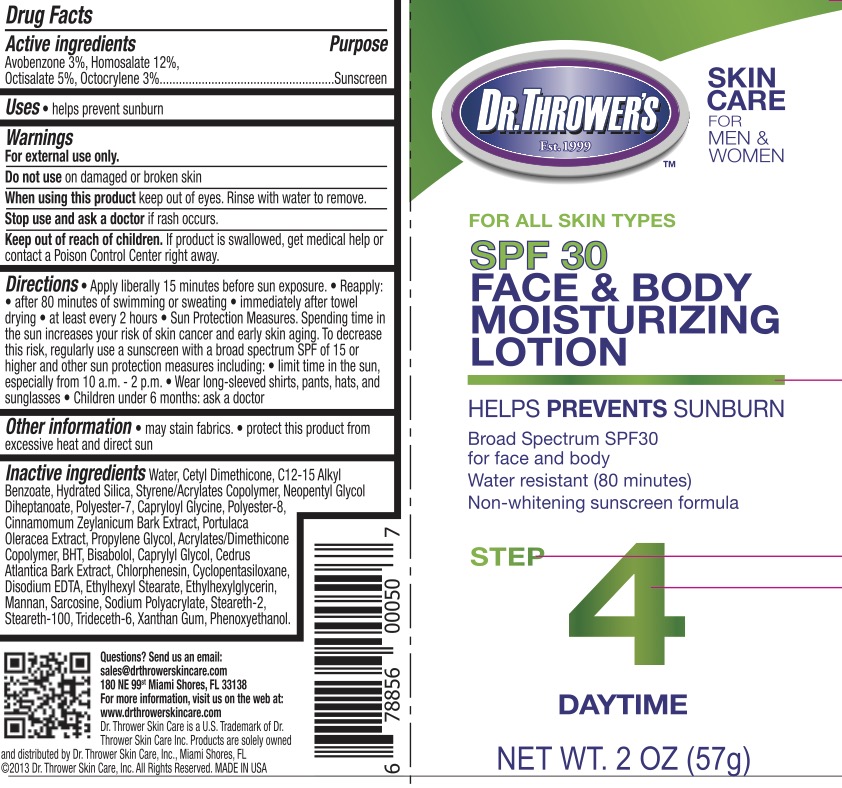 DRUG LABEL: Dr. Throwers SPF 30 Face and Body Sunscreen
NDC: 72839-605 | Form: LOTION
Manufacturer: Derma Care Research Labs, LLC
Category: otc | Type: HUMAN OTC DRUG LABEL
Date: 20241219

ACTIVE INGREDIENTS: OCTISALATE 5 g/100 g; AVOBENZONE 3 g/100 g; OCTOCRYLENE 3 g/100 g; HOMOSALATE 12 g/100 g
INACTIVE INGREDIENTS: CAPRYLYL GLYCOL; STEARETH-100; PURSLANE; EDETATE DISODIUM; CINNAMON BARK OIL; POLYESTER-8 (1400 MW, CYANODIPHENYLPROPENOYL CAPPED); CETYL DIMETHICONE 25; ALKYL (C12-15) BENZOATE; ETHYLHEXYLGLYCERIN; HYDRATED SILICA; BUTYL METHACRYLATE/METHYL METHACRYLATE/METHACRYLIC ACID/STYRENE CROSSPOLYMER; NEOPENTYL GLYCOL DIHEPTANOATE; POLYESTER-7; CAPRYLOYL GLYCINE; WATER; LEVOMENOL; PPG-1 TRIDECETH-6; XANTHAN GUM; 2-ETHYLHEXYL ACRYLATE, METHACRYLATE, METHYL METHACRYLATE, OR BUTYL METHACRYLATE/HYDROXYPROPYL DIMETHICONE COPOLYMER (30000-300000 MW); CHLORPHENESIN; SARCOSINE; CEDRUS ATLANTICA BARK; STEARETH-2; PHENOXYETHANOL; SODIUM POLYACRYLATE (8000 MW); YEAST MANNAN; PROPYLENE GLYCOL; CYCLOMETHICONE 5

Dr. Thrower's SPF 30 Face and Body Sunscreen Lotion

Active Ingredients

Avobenzone 3%, Homosalate 12%, Octisalate 5%, Octocrylene 3%

Purpose

Sunscreen

Uses

Helps prevent sunburn.

Warnings

For external use only.

Do not use on damaged or broken skin. When using this product keep out of eyes. Rinse eyes with water to remove.

Stop use and ask a doctor if rash occurs.

Keep Out of Reach of Children.

If swallowed, get medical help or contact a Poison Control Center right away.

Directions

Apply liberally 15 minutes before sun exposure. Reapply:

- after 80 minutes of swimming or sweating
- immediately after towel drying
- at least every 2 hours

Sun protection measures: spending time n the sun increases your risk of skin cancer and early skin aging. To decrease risk, regularly use a sunscreen with broad spectrum SPF of 15 or higher and other sun protection measure including:

- limit time in the sun, especially from 10 am to 2 pm
- wear long-sleeved shirts, pants, hats, and sunglasses.
- Children under 6 months: ask a doctor.

Inactive Ingredients

Water, Cetyl Dimethicone, C12-15 Alkyl Benzoate, Hydrated Silica, Styrene/Acrylates Copolymer, Neopentyl Glycol Diheptanoate, Polyester-7, Capryloyl Glycine, Polyester-8, Cinnamomum Zeylanicum Bark Extract, Portulaca Oleracea Extract, Propylene Glycol, Acrylates/Dimethicone Copolymer, BHT, Bisabolol, Caprylyl Glycol, Cedrus Atlantica Bark Extract, Chlorphenesin, Cyclopentasiloxane, Disodium EDTA, Ethylhexyl Stearate, Ethylhexylglycerin, Mannan, Sarcosine, Sodium Polyacrylate, Steareth-2, Steareth-100, Trideceth-6, Xanthan Gum, Phenoxyethanol.